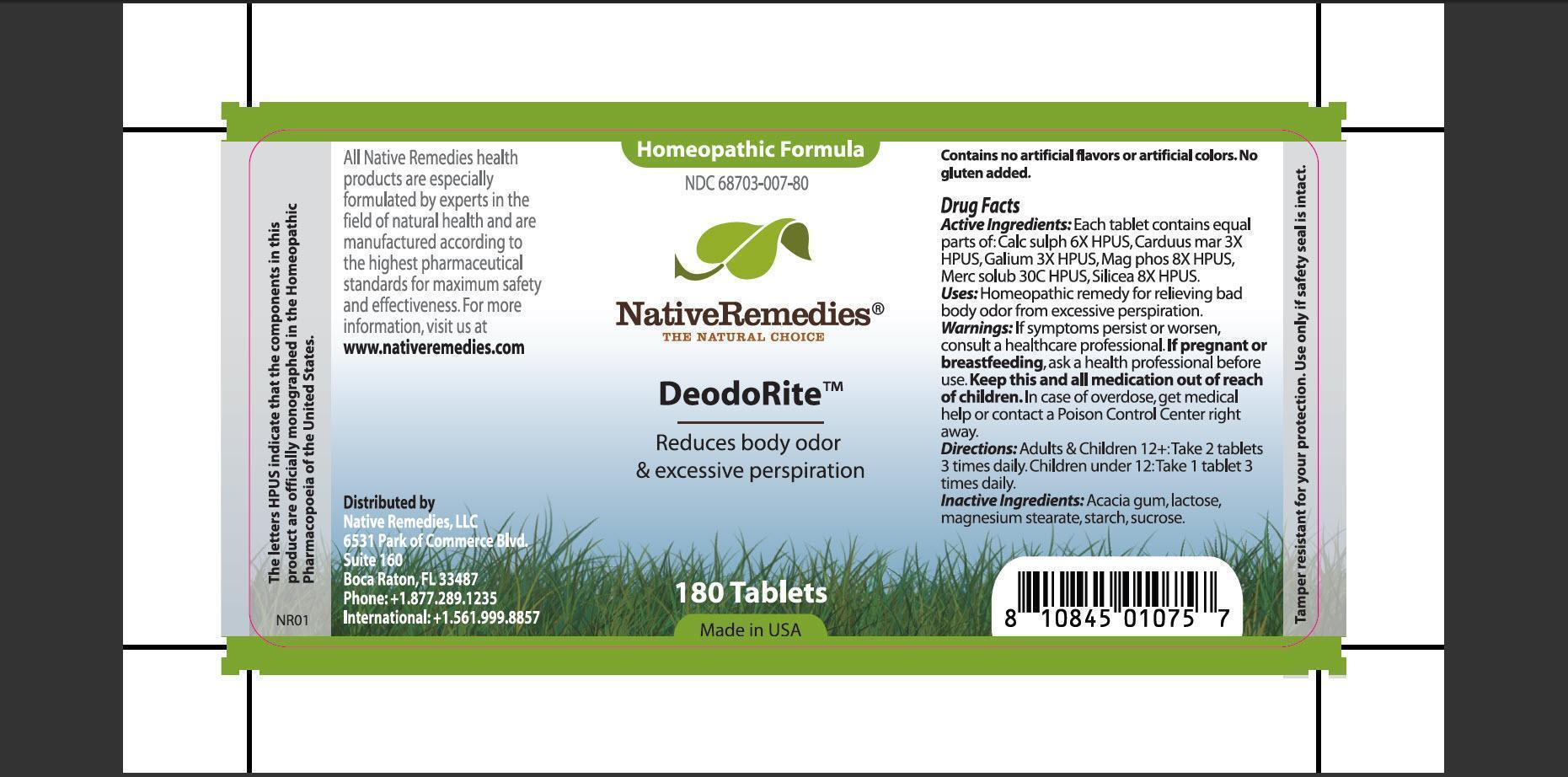 DRUG LABEL: DeodoRite
                
                
NDC: 68703-007 | Form: TABLET
Manufacturer: Native Remedies LLC
Category: homeopathic | Type: HUMAN OTC DRUG LABEL
Date: 20130102

ACTIVE INGREDIENTS: CALCIUM SULFATE ANHYDROUS 6 [hp_X]/1 1; SILYBUM MARIANUM SEED 3 [hp_X]/1 1; GALIUM APARINE 3 [hp_X]/1 1; MAGNESIUM PHOSPHATE, DIBASIC TRIHYDRATE 8 [hp_X]/1 1; MERCURIUS SOLUBILIS 30 [hp_C]/1 1; SILICON DIOXIDE 8 [hp_X]/1 1
INACTIVE INGREDIENTS: ACACIA; LACTOSE; MAGNESIUM STEARATE; STARCH, CORN; SUCROSE

DeodoRite

PURPOSE

Reduces body odor and excessive perspiration

ACTIVE INGREDIENT

Enter section text here

INDICATIONS AND USAGE

Uses: Homeopathic remedy for relieving bad body odor from excessive perspiration.

WARNINGS

Warning: If symptoms persist or worsen, consult a healthcare professional.

PREGNANCY OR BREAST FEEDING

If pregnant or breastfeeding, ask a health professional before use.

KEEP OUT OF REACH OF CHILDREN

Keep this and all medication out of reach of children.

OVERDOSAGE

In case of overdose, get medical help or contact a Poison Control Center right away.

DOSAGE AND ADMINISTRATION

Directions: Adults and Children 12+: Take 2 tablets 3 times daily. Children under 12: Take 1 tablet 3 times daily.

INACTIVE INGREDIENT

Inactive Ingredients: Acacia gum, lactose, magnesium stearate, starch, sucrose.

PATIENT COUNSELING INFORMATION

The letters HPUS indicate that the components in this product are officially monographed in the Homeopathic Pharmacopoeia of the United States.

All Native Remedies health products are especially formulated by experts in the field of natural health and are manufactured according to the highest pharmaceutical standards for maximum safety and effectiveness. For more information, visit us at www.nativeremedies.com

Distributed by
Native Remedies, LLC
6531 Park of Commerce Blvd.
Suite 160
Boca Raton, Fl 33487
Phone:+1.877.289.1235
International:+1.561.999.8857

Contains no artificial flavors or artificial colors. No gluten added.

STORAGE AND HANDLING

Tamper resistant for your protection. Use only if safety seal is intact.